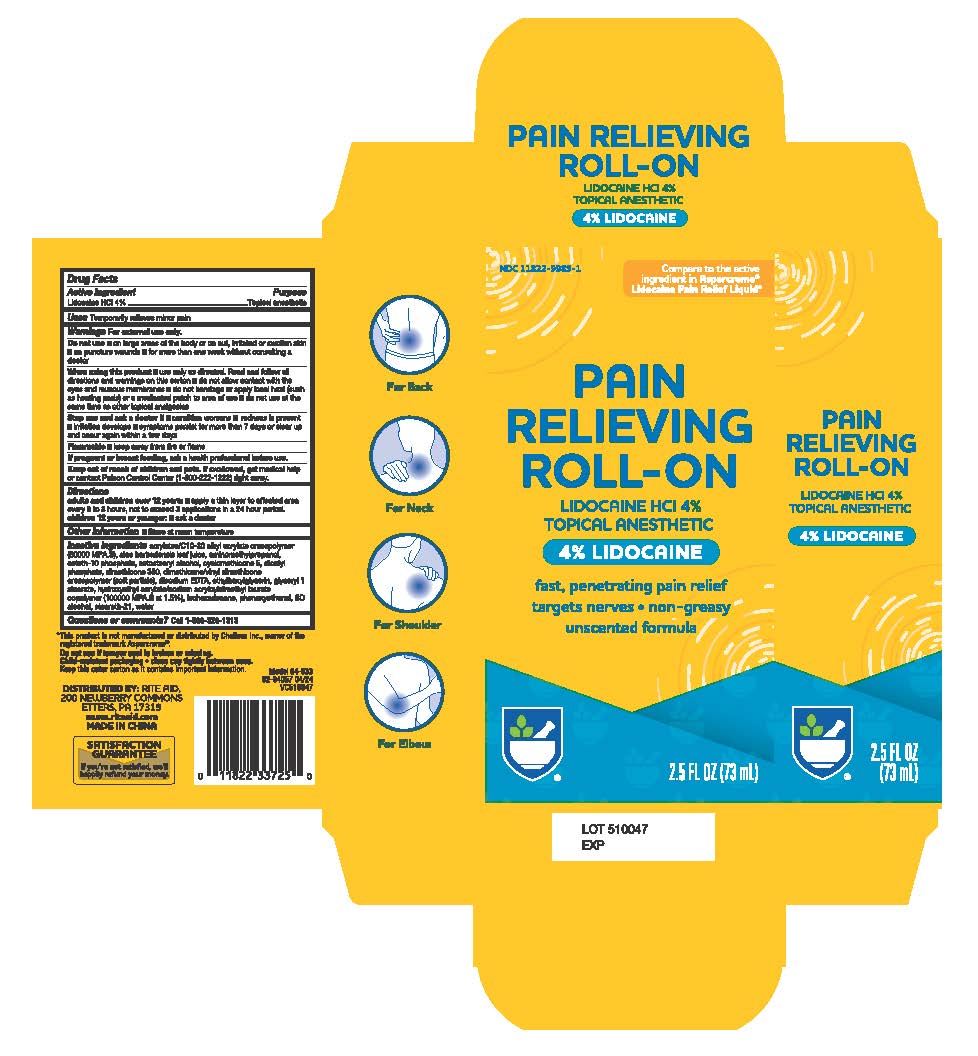 DRUG LABEL: Rite Aid Pain Relieving Roll-On
NDC: 11822-9989 | Form: LIQUID
Manufacturer: Rite Aid Corporation
Category: otc | Type: HUMAN OTC DRUG LABEL
Date: 20240816

ACTIVE INGREDIENTS: LIDOCAINE 4 g/1 mL
INACTIVE INGREDIENTS: ACRYLATES/C10-30 ALKYL ACRYLATE CROSSPOLYMER (60000 MPA.S); ALOE VERA LEAF; PHENOXYETHANOL; CETOSTEARYL ALCOHOL; ETHYLHEXYLGLYCERIN; CYCLOMETHICONE 5; DIHEXADECYL PHOSPHATE; ISOHEXADECANE; STEARETH-21; GLYCERYL 1-STEARATE; AMINOMETHYLPROPANOL; WATER; HYDROXYETHYL ACRYLATE/SODIUM ACRYLOYLDIMETHYL TAURATE COPOLYMER (45000 MPA.S AT 1%); CETETH-10 PHOSPHATE; EDETATE DISODIUM ANHYDROUS; DIMETHICONE/VINYL DIMETHICONE CROSSPOLYMER (SOFT PARTICLE); DIMETHICONE 350; ALCOHOL

Rite Aid Pain Relieving Roll-On with 4% Lidocaine, 2.5 oz

ACTIVE INGREDIENT

Lidocaine HCl 4%

PURPOSE

Topical Anesthetic

Uses

Temporarily relieves minor pain

Warning

For External use only

Do not use■on large areas of the body or on cut, irritated or swollen skin ■on puncture wounds ■ for more than one week without consulting a doctor

When using this product

■use only as directed. Read and follow all directions and warnings on this carton

■ do not allow contact with the eyes and mucous membranes

■do not bandage or apply local heat (such as heating pads) or a medicated patch to area of use

■do not use at the same time as other topical analgesics

Stop use and ask a doctor if

■condition worsens ■ redness is present
■irritation develops

■symptoms persist for more than 7 days or clear up and occur again within a few days

OTHER SAFETY INFORMATION

Flammable

Keep away from fire or flame

Store at room temperature

PREGNANCY OR BREAST FEEDING

If pregnant or breast feeding, ask a health professional before use

Keep out if reach of children and pets

If swallowed, get medical help or contact Poison Control Center (1-800-222-1222) right away

Directions

adults and children over 12 years:■apply a thin layer to affected area every 6 to 8 hours, not to
exceed 3 applications in a 24 hour period.
children 12 years or younger: ■ask a doctor

INACTIVE INGREDIENT

Inactive ingredients acrylates/C10-30 alkyl acrylate crosspolymer (60000 MPA.S), aloe barbadensis leaf juice, amynomethylpropanol, cetelh-10 phosphate, cetostearyl alcohol, cyclomethicone 5, dicetyl phosphate, dimethicone 350, dimethicone/vinyl dimethicone
crosspolymer (soft particle), disodium EDTA, ethylhexylglycerin, glyceryl 1 stearate, hydroxyethyl acrylate/sodium acryloyldimethyl taurate copolymer (100000 MPA.S at 1.5%), sohexadecane, phenoxyethanol, SD alcohol, steareth-21, water

QUESTIONS

Call 1-866-326-1313